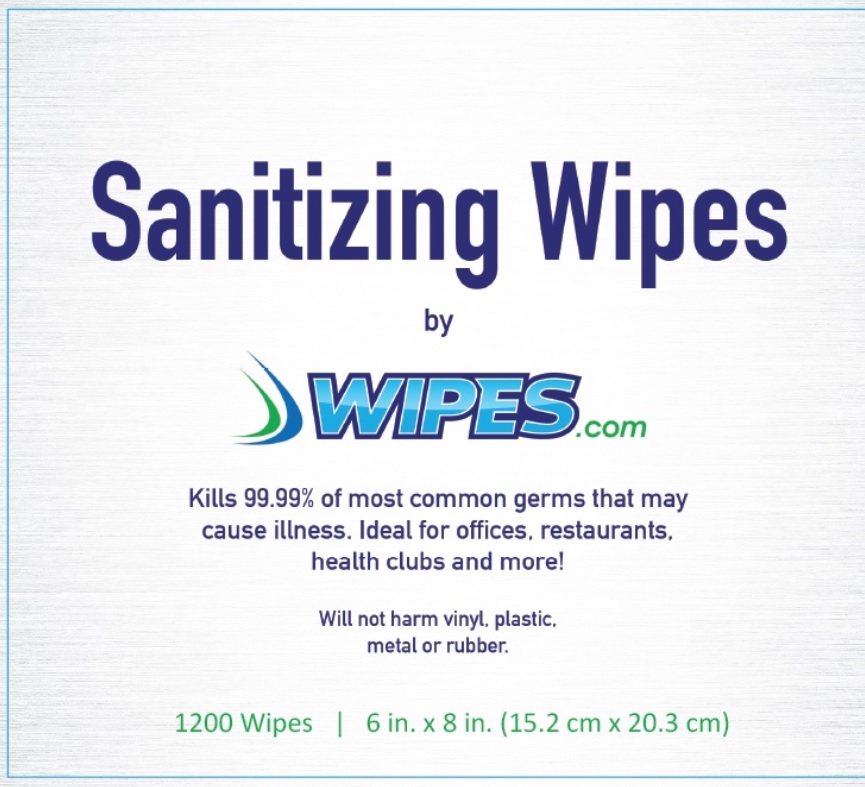 DRUG LABEL: Sanitizing Wipes
NDC: 70972-1200 | Form: SWAB
Manufacturer: Wipes LLC
Category: otc | Type: HUMAN OTC DRUG LABEL
Date: 20251219

ACTIVE INGREDIENTS: BENZALKONIUM CHLORIDE 0.13 g/100 g
INACTIVE INGREDIENTS: WATER; PHENOXYETHANOL; DECYL GLUCOSIDE; POTASSIUM SORBATE; SODIUM BENZOATE; EDETATE DISODIUM; CITRIC ACID MONOHYDRATE; ALOE VERA LEAF

Drug Facts

Active ingredient

Benzalkonium chloride 0.13%

Purpose

Antimicrobial

Uses

- For hand sanitizing to decrease bacteria on the skin
- Recommended for repeated use

Warnings

For external use only

Do not use if

you are allergic to any of this ingredients

When using this product

avoid contact with eyes. In case of eye contact, flush eyes with water.

Stop use and ask a doctor

If irriatation or redness develops, or if condition persists for more than 72 hours.

Keep out of reach of children

If swallowed, get medical help or contact a Poison Control Center right away.

Directions

Adults and Children 2 Years and Over: Apply to hands. Allow to dry without wiping.

Children under 2 Years: Ask a doctor before use

To dispense: Pull tab and remove large cover. Insert triangular threading loop through slits in cover. Do not push finger through the opening. Thread first sheet in center of roll through loop. Replace cover. Pull loop back through opening. Pull each sheet up and slightly to the side. Dispose of wipe in trash. DO NOT FLUSH.

Other information

Store below 95oF (35oC). keep closed tightly. May discolor certain fabric or surfaces

Inactive ingredients

Water, SD Alcohol 40, Phenoxyethanol, Decyl Glucoside, Potassium Sorbate, Sodium Benzoate, Disodium EDTA, Citric Acid, Aloe Barbadensis (Aloe) Leaf Extract, Fragrance

Principal Display Panel

NDC 70792-1200-1

Sanitizing Wipes by WIPES.com

Kills 99.99% of most common germs that may cause illness. Ideal for offices, restaurants, health clubs and more!

Will not harm vinyl, plastic, metal and rubber

1200 Wipes

6 in. x 8 in. (15.2 cm x 20.3 cm)